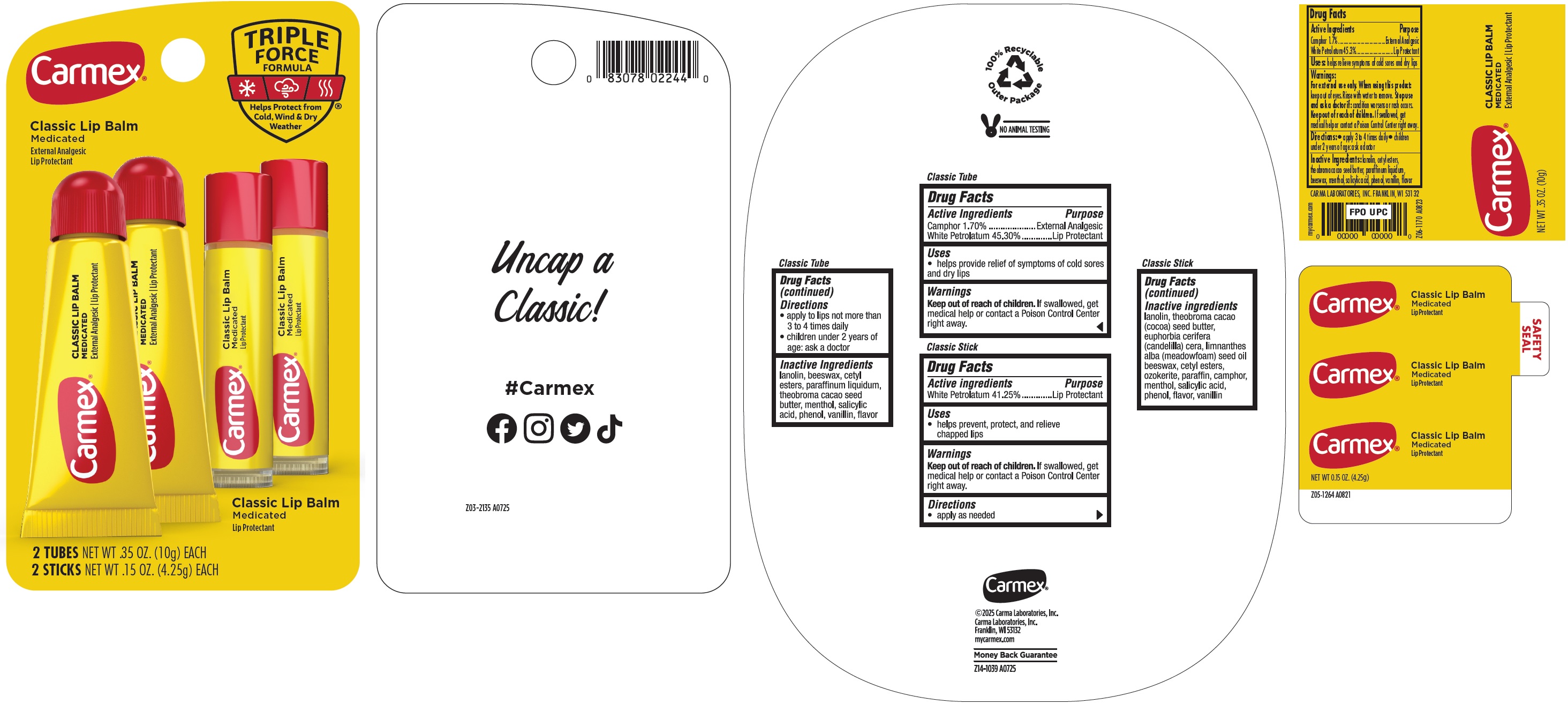 DRUG LABEL: Carmex Classic Lip Balm Medicated
NDC: 10210-0096 | Form: KIT | Route: TOPICAL
Manufacturer: Carma Laboratories, Inc.
Category: otc | Type: HUMAN OTC DRUG LABEL
Date: 20251001

ACTIVE INGREDIENTS: CAMPHOR (SYNTHETIC) 1.7 g/100 g; WHITE PETROLATUM 45.3 g/100 g; WHITE PETROLATUM 412.5 mg/1 g
INACTIVE INGREDIENTS: LANOLIN; YELLOW WAX; CETYL ESTERS WAX; MINERAL OIL; MENTHOL, UNSPECIFIED FORM; SALICYLIC ACID; PHENOL; VANILLIN; LANOLIN; COCOA BUTTER; CETYL ESTERS WAX; PARAFFIN; CAMPHOR (SYNTHETIC); MENTHOL; SALICYLIC ACID; PHENOL; VANILLIN

Carmex Classic Lip Balm Medicated

Active Ingredients

Camphor 1.70%
White Petrolatum 45.30%

Purpose

External Analgesic
Lip Protectant

Uses

- helps provide relief of symptoms of cold sores and dry lips

Warnings

Keep out of reach of children.

If swallowed, get medical help or contact a Poison Control Center right away.

Directions

- apply to lips not more than 3 to 4 times daily
- children under 2 years of age: ask a doctor

Inactive Ingredients

lanolin, beeswax, cetyl esters, paraffinum liquidum, theobroma cacao seed butter, menthol, salicylic acid, phenol, vanillin, flavor

Active ingredients

White Petrolatum 41.25%

Purpose

Lip Protectant

Uses

- helps prevent, protect, and relieve chapped lips

Warnings

Keep out of reach of children.

If swallowed, get medical help or contact a Poison Control Center right away.

Directions

- apply as needed

Inactive ingredients

lanolin, theobroma cacao (cocoa) seed butter, euphorbia cerifera (candelilla) cera, limnanthes alba (meadowfoam) seed oil beeswax, cetyl esters, ozokerite, paraffin, camphor, menthol, salicylic acid, phenol, flavor, vanillin